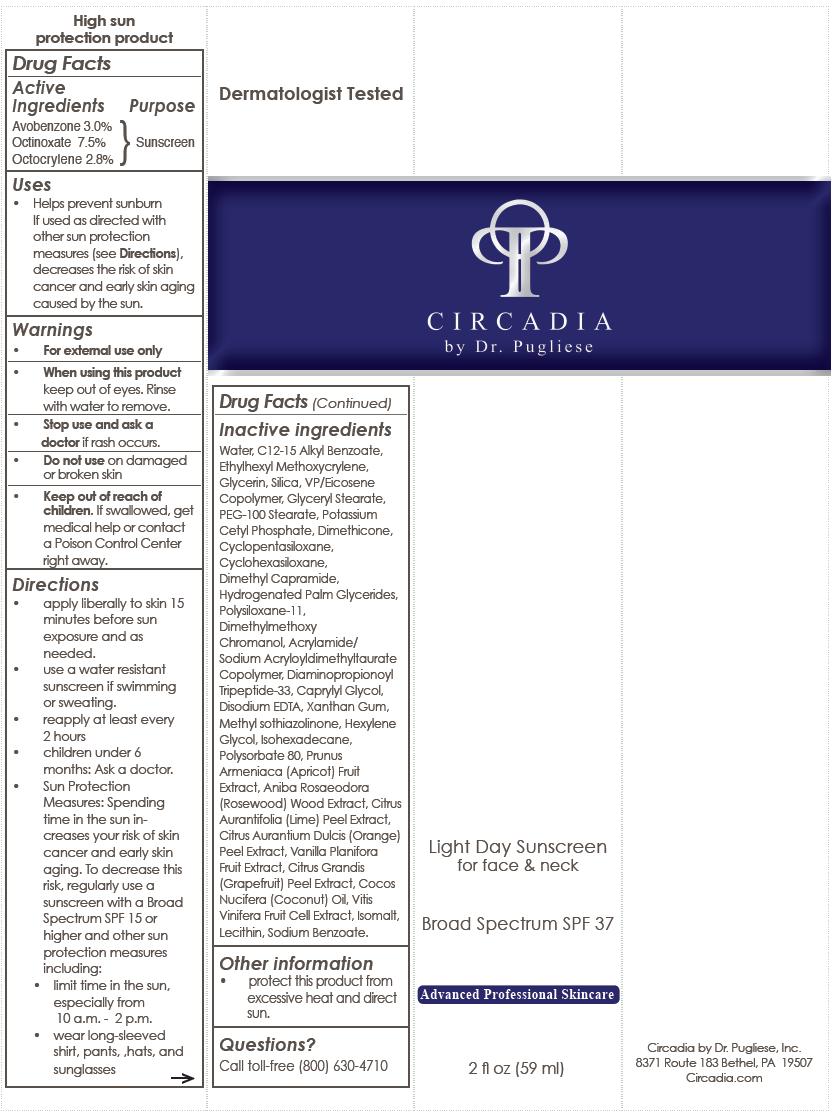 DRUG LABEL: Light Day Sunscreen Broad Spectrum SPF 37
NDC: 76458-201 | Form: LOTION
Manufacturer: Circadia by Dr Pugliese, Inc.
Category: otc | Type: HUMAN OTC DRUG LABEL
Date: 20120830

ACTIVE INGREDIENTS: AVOBENZONE 0.03 mL/1 mL; OCTINOXATE 0.075 mL/1 mL; OCTOCRYLENE 0.028 mL/1 mL
INACTIVE INGREDIENTS: WATER; ALKYL (C12-15) BENZOATE; GLYCERIN; SILICON DIOXIDE; GLYCERYL MONOSTEARATE; PEG-100 STEARATE; POTASSIUM CETYL PHOSPHATE; DIMETHICONE; CYCLOMETHICONE 5; CYCLOMETHICONE 6; DIMETHYL CAPRAMIDE; HYDROGENATED PALM GLYCERIDES; SODIUM ACRYLATE/SODIUM ACRYLOYLDIMETHYLTAURATE COPOLYMER (4000000 MW); CAPRYLYL GLYCOL; EDETATE DISODIUM; XANTHAN GUM; METHYLISOTHIAZOLINONE; HEXYLENE GLYCOL; ISOHEXADECANE; POLYSORBATE 80; ISOMALT; APRICOT; SODIUM BENZOATE; ANIBA ROSAEODORA WOOD; LIME PEEL; ORANGE PEEL; VANILLA; CITRUS MAXIMA FRUIT RIND; COCONUT OIL; EGG PHOSPHOLIPIDS; WINE GRAPE

Light Day Sunscreen

Active ingredient

Avobenzone 3.0%

Octinoxate 7.5%

Octocrylene 2.8%

Purpose

Sunscreen

Uses

- Helps prevent sunburn if used as directed with other sun protection measures
  (see Directions), decreases the risk of skin cancer and early skin aging caused by the sun.

Warnings

- For external use only
- When using this product keep out of eyes. Rinse with water to remove.
- Stop use and ask a doctor if rash occurs.
- Do not use on damaged or broken skin
- Keep out of reach of children. If swallowed, get medical help or contact a Poison Control Center right away.

Directions

- apply liberally to skin 15 minutes before sun exposure and as
  needed.
- use a water resistant sunscreen if swimming or sweating.
- reapply at least every 2 hours.
- children under 6 months: Ask a doctor.
- Sun Protection Measures: Spending time in the sun increases your risk of skin cancer and early skin aging. To decrease this risk, regularly use a sunscreen with a Broad Spectrum SPF 15 or higher and other sun protection measures including:
  - limit time in the sun, especially from 10 a.m. - 2 p.m.
  - wear long-sleeved shirt, pants, hats, and sunglasses

Inactive ingredients

Water, C12-15 Alkyl Benzoate, Ethylhexyl Methoxycrylene, Glycerin, Silica, Eicosene Copolymer, Glyceryl Stearate, PEG-100 Stearate, Potassium Cetyl Phosphate, Dimethicone, Cyclopentasiloxane, Cyclohexasiloxane, Dimethyl Capramide, Hydrogenated Palm Glycerides, Polysiloxane 11, Dimethylmethoxy Chromanol, Acrylamide/Sodium Acryloyldimethyl Taurate Copolymer, Diaminopropionoyl Tripeptide-33, Caprylyl Glycol, Disodium EDTA, Xanthan Gum, Methylisothiazolinone, Hexylene Glycol, Isohexadecane, Polysorbate 80, Vitis Vinifera Fruit Cell Extract, Isomalt, Prunus Armeniaca (Apricot) Fruit Extract, Lecithin, Sodium Benzoate, Aniba Rosaeodora (Rosewood) Wood Extract, Citrus Aurantifolia (Lime) Peel Extract, Citrus Aurantium Dulcis (Orange) Peel Extract, Vanilla Planifolia Fruit Extract, Citrus Grandis (Grapefruit) Peel Extract, Cocos Nucifera (Coconut) Oil

Other Information

- protect this product from excessive heat and direct sun.

Questions?

Call toll-free (800) 630-4710

Package/Label Principal Display Panel

Light Day Sunscreen for face & neck

Broad Spectrum SPF37

Advanced Professional Skincare

2 fl oz (59 ml)

Circadia by Dr. Pugliese, Inc.
8371 Route 183 Bethel, PA 19507
Circadia.com

Bottle Label